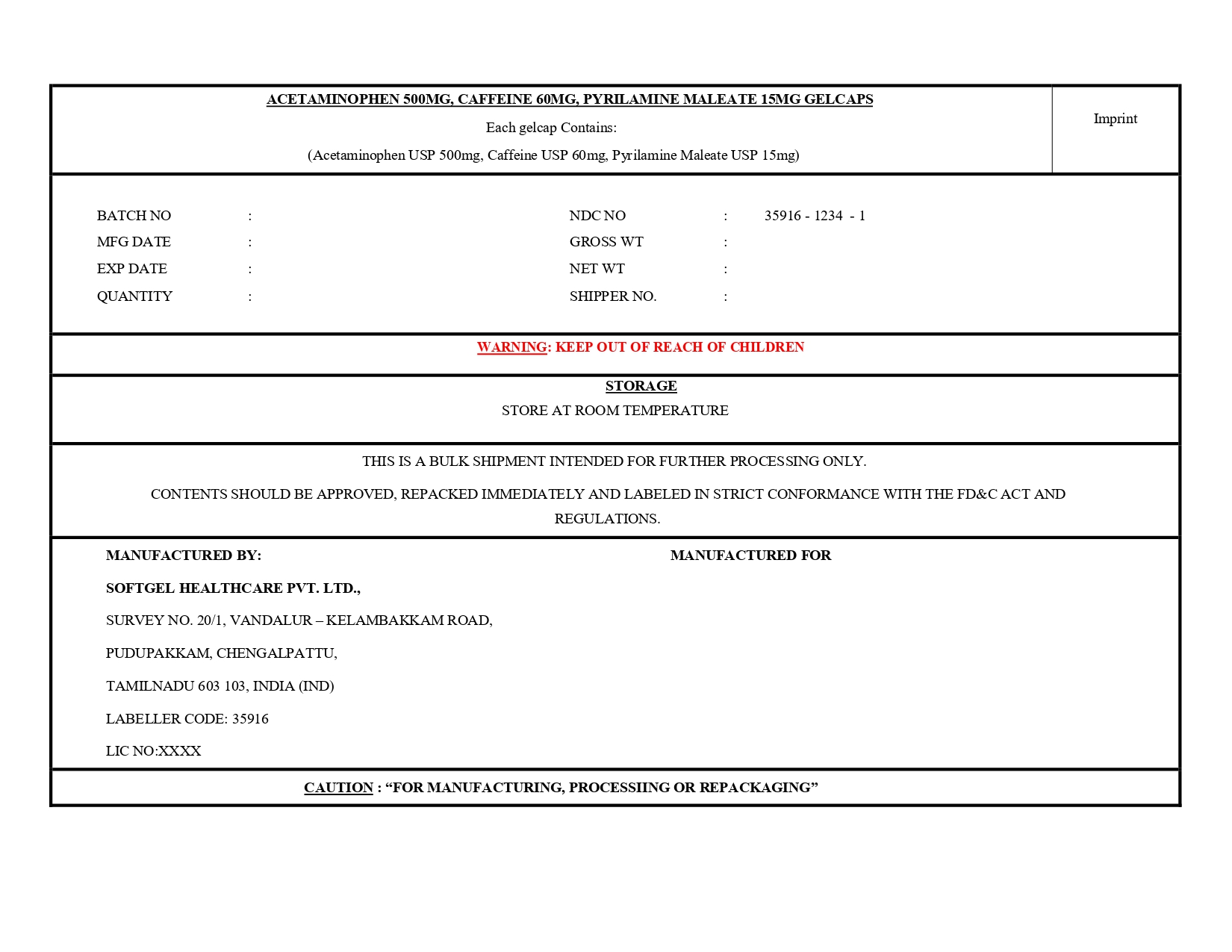 DRUG LABEL: Acetaminophen , Caffeine and pyrilamine maleate
NDC: 35916-1234 | Form: CAPSULE
Manufacturer: Softgel Healthcare Pvt Ltd
Category: otc | Type: HUMAN OTC DRUG LABEL
Date: 20260209

ACTIVE INGREDIENTS: CAFFEINE 60 mg/1 1; PYRILAMINE MALEATE 15 mg/1 1; ACETAMINOPHEN 500 mg/1 1
INACTIVE INGREDIENTS: CROSCARMELLOSE SODIUM; WATER; ISOPROPYL ALCOHOL; MICROCRYSTALLINE CELLULOSE; D&C RED NO. 33 ALUMINUM LAKE; STARCH, POTATO; GELATIN, UNSPECIFIED; GLYCERIN; ETHYLCELLULOSE, UNSPECIFIED; HYPROMELLOSE, UNSPECIFIED; TITANIUM DIOXIDE; SORBITOL; SORBITAN; TALC; TRIACETIN; MAGNESIUM STEARATE; POVIDONE K30; FD&C BLUE NO. 1 ALUMINUM LAKE

Acetaminophen 500mg, Caffeine 60mg, Pyrilamine Maleate 15mg gelcaps

Active ingredient (in each gelcap)

Acetaminophen USP 500mg
Caffeine USP 60mg
Pyrilamine maleate USP 15mg

purpose

- Pain reliever
- Diuretic
- Antihistamine

Uses

for the temporary relief of these symptoms associated with menstural periods:

• cramps

• bloating

• waterweight gain

• headache

• backache

• muscle aches

• fatigue

Warnings

Liver warning: This product contains acetaminophen. Severe liver damage may occur if you take
• more than 6 gelcap in 24 hours, which is the maximum daily amount for this product
• with other drugs containing acetaminophen
• 3 or more alcoholic drinks every day while using this product

Allergy alert: Acetaminophen may cause severe skin or severe allergic reactions.
Symptoms may include: • hives • blisters • rash • skin reddening • facial swelling • asthma (wheezing) • shock
If a skin or general allergic reaction occurs, stop use and seek medical help right away.

Do not use

• with any other drug containing acetaminophen (prescription or nonprescription). If you are not sure whether a drug contains acetaminophen, ask a doctor or pharmacist
• if you have ever had an allergic reaction to this product or any of its ingredients

Ask a doctor before use if you have

• liver disease

• glaucoma

• difficulty in urination due to enlargement of the prostate gland

• a breathing problem such as emphysema or chronic bronchitis

Ask a doctor or pharmacist before use if you are
• taking the blood thinning drug warfarin
• taking sedatives or tranquilizers

When using this product
• you may get drowsy
• avoid alcoholic drinks
• excitability may occur, especially in children
• alcohol, sedatives, and tranquilizers may increase drowsiness
• be careful when driving a motor vehicle or operating machinery
• limit the use of caffeine-containing medications, foods, or beverages beacuse too much caffeine may cause nervousness, irritability, sleeplessness, and, occasionally, rapid heartbeat. The recommended dose of this product contains about as much caffeine as a cup of coffee.

Stop use and ask a doctor if
• new symptoms occur
• redness or swelling is present
• pain gets worse or lasts more than 10 days
• fever gets worse or lasts more than 3 days

PREGNANCY OR BREAST FEEDING

If pregnant or breast-feeding, ask a health professional before use

Keep out of reach of children.

Overdose warning: In case of overdose, get medical help or contact a Poison Control Center right away.
Prompt medical attention is critical for adults as well as children even if you do not notice any signs or symptoms.

Directions
• do not take more than the recommended dose
• adults and children 12 years and older: take 2 gelcap with water
• repeat every 6 hours as needed
• do not exceed 6 gelcap per day
• children under 12 years: consult a doctor

OTHER SAFETY INFORMATION

store at room temperature.

Inactive ingredients

croscarmellose sodium, D&C red 33 aluminum lake, edible black printing ink, ethyl cellulose, FD&C blue 1 aluminum lake, gelatin, glycerin, hydroxypropyl methylcellulose, isopropyl alcohol, magnesium stearate, microcrystalline cellulose, pregelatinized potato starch, purified water, PVPK-30, sorbitol sorbitan solution, talc, titanium dioxide, triacetin.